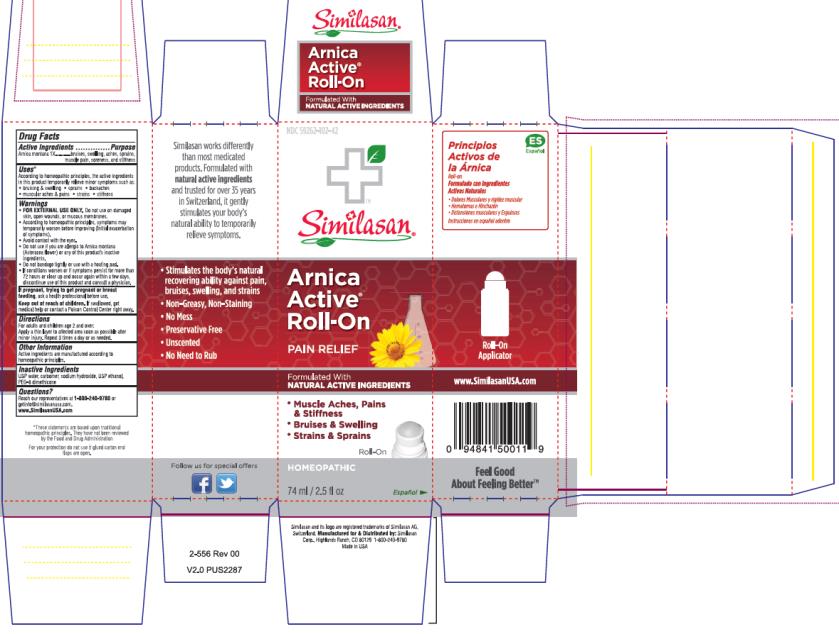 DRUG LABEL: Arnica Active Roll-On
NDC: 59262-102 | Form: LIQUID
Manufacturer: Similasan Corporation
Category: homeopathic | Type: HUMAN OTC DRUG LABEL
Date: 20161212

ACTIVE INGREDIENTS: ARNICA MONTANA 1 [hp_X]/1 mL
INACTIVE INGREDIENTS: WATER; CARBOXYPOLYMETHYLENE; SODIUM HYDROXIDE; ALCOHOL; PEG-8 DIMETHICONE

Arnica Active Roll-On

Arnica Active® Roll-On

Drug Facts

Active Ingredients

Arnica montana 1X

Purpose

bruises, swelling, aches, sprains, muscle pain, soreness, and stiffness

Uses*

According to homeopathic principles, the active ingredients in this product temporarily relieve minor symptoms such as:
• bruising & swelling
• sprains
• backaches
• muscular aches & pains
• strains
• stiffness

Warnings

• FOR EXTERNAL USE ONLY. Do not use on damaged skin, open wounds, or mucous membranes.

• According to homeopathic principles, symptoms may temporarily worsen before improving (Initial exacerbation of symptoms).

• Avoid contact with the eyes.

• Do not use if you are allergic to Arnica montana (Asteracea flower) or any of this product’s inactive ingredients.

• Do not bandage tightly or use with a heating pad.

• If conditions worsen or if symptoms persist for more than 72 hours or clear up and occur again within a few days, discontinue use of this product and consult a physician.

Keep out of reach of children.

If swallowed, get medical help or contact a Poison Control Center right away.

Directions

For adults and children age 2 and over:

Apply a thin layer to affected area soon as possible after minor injury. Repeat 3 times a day or as needed.

Other Information

Active ingredients are manufactured according to homeopathic principles.

Inactive Ingredients

USP water, carbomer, sodium hydroxide, USP ethanol, PEG-8 dimethicone

Questions?

Reach our representatives at 1-800-240-9780 or getinfo@similasanusa.com.

www.SimilasanUSA.com

*These statements are based upon traditional homeopathic principles. They have not been reviewed by the Food and Drug Administration

PRINCIPAL DISPLAY PANEL

NDC 59262-102-42
Similasan
Arnica
Active
Roll-On
Pain Relief
74 ml/ 2.5 fl oz